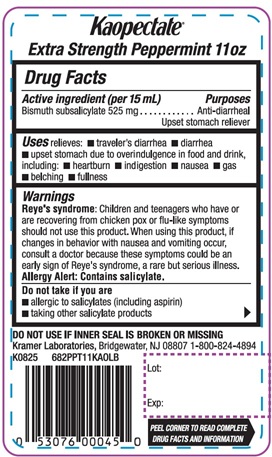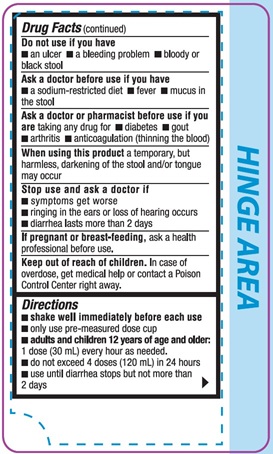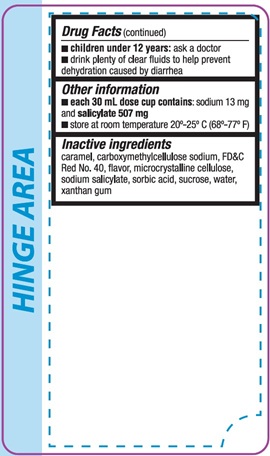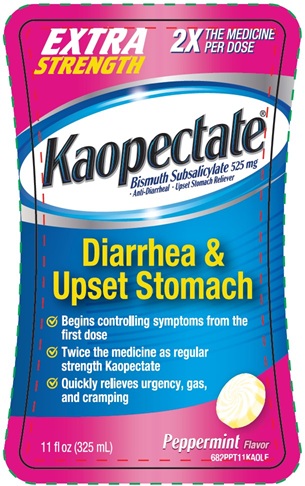 DRUG LABEL: Kaopectate
NDC: 55505-229 | Form: LIQUID
Manufacturer: KRAMER LABORATORIES
Category: otc | Type: HUMAN OTC DRUG LABEL
Date: 20251015

ACTIVE INGREDIENTS: Bismuth Subsalicylate 525 mg/15 mL
INACTIVE INGREDIENTS: Caramel; Carboxymethylcellulose Sodium, Unspecified; Fd&C Red No. 40; Microcrystalline Cellulose; Sodium Salicylate; Sorbic Acid; Sucrose; Water; Xanthan Gum

Kaopectate®
Extra Strength Peppermint 11oz
Drug Facts

Active Ingredient (per 15 mL)

Bismuth subsalicylate 525 mg

Purposes

Anti-diarrheal
Upset stomach reliever

Uses

relieves:

- traveler's diarrhea
- diarrhea
- upset stomach due to overindulgence in food and drink

including:

- heartburn
- indigestion
- nausea
- gas
- belching
- fullness

Warnings

Reye's syndrome: Children and teenagers who have or are recovering from chicken pox or flu-like symptoms should not use this product. When using this product, if changes in behavior with nausea and vomiting occur, consult a doctor because these symptoms could be an early sign of Reye's syndrome, a rare but serious illness.
Allergy Alert: Contains salicylate.

Do not take if you are

- allergic to salicylates (including aspirin)
- taking other salicylate products

Do not use if you have

- an ulcer
- a bleeding problem
- bloody or black stool

Ask a doctor before use if you have

- a sodium-restricted diet
- fever
- mucus in the stool

Ask a doctor or pharmacist before use if you are

taking any drug for

- diabetes
- gout
- arthritis
- anticoagulation (thinning the blood)

When using this product

a temporary, but harmless, darkening of the stool and/or tongue may occur

Stop use and ask a doctor if

- symptoms get worse
- ringing in the ears or loss of hearing occurs
- diarrhea lasts more than 2 days

If pregnant or breast-feeding

ask a health professional before use.

Keep out of reach of children

In case of overdose, get medical help or contact a Poison Control Center right away.

Directions

- shake well immediately before each use
- only use pre-measured dose cup
- adults and children 12 years of age and older: 1 dose (30 mL) every hour as needed.
- do not exceed 4 doses (120 mL) in 24 hours
- use until diarrhea stops but not more than 2 days
- children under 12 years: ask a doctor
- drink plenty of clear fluids to help prevent dehydration caused by diarrhea

Other information

- each 30 mL dose cup contains: sodium 13 mg and salicylate 507 mg
- store at room temperature 20°-25° C (68°-77° F)

Inactive ingredients

caramel, carboxymethylcellulose sodium, FD&C Red No. 40, flavor, microcrystalline cellulose, sodium salicylate, sorbic acid, sucrose, water, xanthan gum

Principal Display Panel

EXTRA
STRENGTH
2X
THE MEDICINE
PER DOSE
Kaopectate®
Bismuth Subsalicylate 525 mg
● Anti-Diarrheal ● Upset stomach Reliever
Diarrhea &
Upset Stomach
√ Begins controlling symptoms from the first dose
√ Twice the medicine as regular strength Kaopectate
√ Quickly relieves urgency, gas, and cramping
11 fl oz (325 mL)
Peppermint Flavor
682PPT11KA0LB

DO NOT USE IF INNER SEAL IS BROKEN OR MISSING
Kramer Laboratories, Bridgewater, NJ 08807 1-800-824-4894
K0825 682PPT11KA0LB
Lot:
Exp:
PEEL CORNER TO READ
DRUG FACTS AND INFORMATION